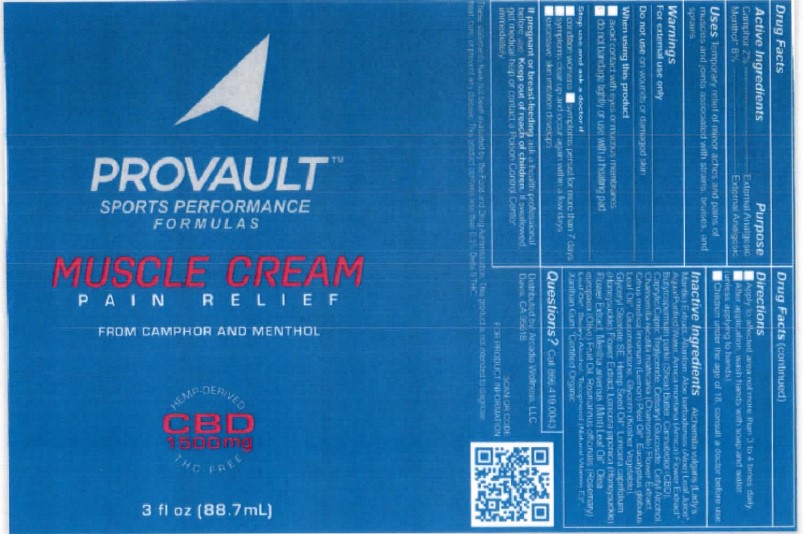 DRUG LABEL: Provault Muscle Cream CBD
NDC: 61577-6200 | Form: CREAM
Manufacturer: Sombra Cosmetics Inc
Category: otc | Type: HUMAN OTC DRUG LABEL
Date: 20221018

ACTIVE INGREDIENTS: MENTHOL .08 g/1 g; CAMPHOR (SYNTHETIC) .02 g/1 g
INACTIVE INGREDIENTS: WATER; GLYCERIN; CANNABIDIOL; TOCOPHEROL; XANTHAN GUM; ALLANTOIN; ALOE VERA LEAF; CETEARYL GLUCOSIDE; GLYCERYL STEARATE SE; CETYL ALCOHOL; OLIVE OIL; SHEA BUTTER; STEARYL ALCOHOL; GLUCONOLACTONE; ROSEMARY OIL; LEMON OIL; CHAMOMILE; EUCALYPTUS OIL; hemp; MENTHA ARVENSIS FLOWER OIL; ARNICA MONTANA FLOWER WATER; LONICERA JAPONICA FLOWER; CAPRYLIC/CAPRIC/LINOLEIC TRIGLYCERIDE

Provault Muscle Cream CBD

Active Ingredients

Menthol USP 8%, Camphor USP 2%

Purpose

External Analgesic

Keep out of reach of children

Uses

Temporary relief of monor aches and pains of muscles and joints associated with strains, bruises and sprains.

Warnings

For external use only.

Directions

Apply to affected area not more than 3 to 4 times daily. After each application, wash hands with soap and water (unless applying to hands). Children under the age of 18, consult a doctor before use.

Inactive Ingredients

Alchemilla Vulgaris (Lady's Mantle) Extract, Allantoin, Aloe Barbadensis (Aloe) Leaf Juice, Aqua/Purified Water, Arnica Montana (Arnica) Flower Extract, Butyrospermum Parkii (Shea) Butter, Cannabidiol (CBD), Caprylic/Capric Triglyceride, Cetearyl Glucoside, Cetyl Alcohol, Chamomilla Recutita Matricaria (Chamomile) Flower Extract, Citrus medica Limon (Lemon) Peel Oil, Eucalyptus Globulus Leaf Oil, Gluconolactone, Glycerin (Kosher Vegetable), GLyceryl Sterate SE, Hemp Seed Oil, Lonicera Japonica (Honeysuckle) Flower Extract, Mentha Arvensis (mint) Leaf Oil, Olea Europaea (Olive) Fruit Oil, Rosmarinus Officinalis (Rosemary) Leaf Oil, Stearyl Alcohol, Tocopherol (Natural Vitamin E), Xanthan Gum.

Questions or Comments

Call 866 419 0043